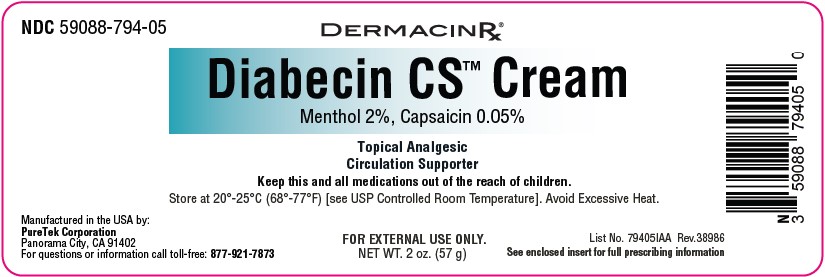 DRUG LABEL: Diabecin CS Cream
NDC: 59088-794 | Form: CREAM
Manufacturer: Puretek Corporation
Category: otc | Type: HUMAN OTC DRUG LABEL
Date: 20250610

ACTIVE INGREDIENTS: CAPSAICIN 0.0005 g/1 g; MENTHOL 0.02 g/1 g
INACTIVE INGREDIENTS: DIMETHICONE; LECITHIN, SOYBEAN; NYLON-12; PEUCEDANUM OSTRUTHIUM LEAF; SODIUM HYALURONATE; LAURETH-7; CARTHAMUS TINCTORIUS (SAFFLOWER) OLEOSOMES; PEG-100 STEARATE; SODIUM ASCORBYL PHOSPHATE; POLYACRYLAMIDE (1500 MW); SILICA; WATER; ARNICA MONTANA FLOWER; GLYCERYL STEARATE; C12-15 ALKYL BENZOATE; GLYCERIN; MYRISTYL MYRISTATE; GINGER; CETEARYL ALCOHOL; IMIDAZOLIDINYL UREA; .ALPHA.-TOCOPHEROL ACETATE, DL-; BISABOLOL; CALENDULA OFFICINALIS FLOWER; ISOPROPYL MYRISTATE; MALTODEXTRIN; NIACINAMIDE; PHENOXYETHANOL; CHAMOMILE; ESCIN; ALUMINUM STARCH OCTENYLSUCCINATE; BETA-SITOSTEROL; PYRIDOXINE HCL; ALOE BARBADENSIS LEAF JUICE; C13-14 ISOPARAFFIN; CALCIUM PANTOTHENATE; GINKGO BILOBA LEAF

NDC 59088-794 Diabecin CS Cream

Active ingredient

Menthol 2%
Capsaicin 0.05%

Purpose

Menthol -Topical Analgesic
Capsaicin- Topical Analgesic

Uses

For the temporary relief of minor aches and pains of muscles and joints associated with simple backache, arthritis, strains, bruises, and sprains.

Warnings

For external use only

• This is not a face cream. Do not apply to the face.
• Do not use at the same time with other topical analgesics.
• Do not use if allergic to chili peppers or if past allergic reaction to capsaicin.
• Do not apply to wounds or damaged skin.
• Do not bandage tightly.
• Do not apply within 1 hour before or after bath, shower, hot tub, sauna, or vigorous exercise. Warm water, perspiration, or open pores can intensify the impact of this product and burning sensation.
• Do not use with heating pad, hot water bottle or other source of heat. Doing so can increase risk of serious burn.

When using this product

• Avoid contact with the eyes.

Stop use and ask a doctor if

• condition worsens • symptoms last more than 7 days or clear up and occur again within a few days

Keep out of reach of children.

If swallowed, get medical help or contact a Poison Control Center right away.

Directions

• Adults and children 2 years of age and older: Apply to affected area not more than 3 to 4 times daily. Children under 2 years of age: do not use, consult a doctor.
• Apply sparingly to affected area not more than 4 times daily. However, for first use, apply to small area to test for sensitivity or skin reaction.
• Gently massage into the skin until fully absorbed.
• Wash hands with soap and water thoroughly after each application to avoid spreading to the eyes or other sensitive mucous membranes.

Other information

Store in a cool well-ventilated area away from heat. Keep away from sparks or open flame. Store at 20° to 25°C (68° to 77°F) [see USP Controlled Room Temperature]. Avoid excessive heat. Do not use if package is damaged.

Inactive ingredients:

Aloe Barbadensis (Aloe Vera) Leaf Juice, Aqua (Purified Water), Arnica Montana (Arnica) Flower Extract, Beta-Sitosterol, Bisabolol, C12-15 Alkyl Benzoate, C13-14 Isoparaffin, Calcium Pantothenate (Vitamin B5), Calendula Officinalis (Calendula) Flower Extract, Carthamus Tinctorius (Safflower) Oleosomes, Cetearyl Alcohol, Chamomilla Recutita (Matricaria) Flower Extract, Dimethicone, DL-Alpha-Tocopheryl Acetate (Vitamin E), Escin, Ginkgo Biloba (Ginkgo) Leaf Extract, Glycerin, Glyceryl Stearate, Imidazolidinyl Urea, Isopropyl Myristate, Laureth-7, Lecithin, Maltodextrin, Myristyl Myristate, Niacinamide (Vitamin B3), Nylon-12, PEG-100 Stearate, Peucedanum Ostruthium (Masterwort) Leaf Extract, Phenoxyethanol, Polyacrylamide, Pyridoxine HCl (Vitamin B6), Silica, Sodium Ascorbyl Phosphate (Vitamin C), Sodium Hyaluronate, Sodium Starch Octenylsuccinate, Zingiber Officinale (Ginger) Root Extract.

Diabecin CS™ Cream

Manufactured by:
PureTek Corporation
Panorama City, CA 91402
For questions or information
call toll-free: 877-921-7873